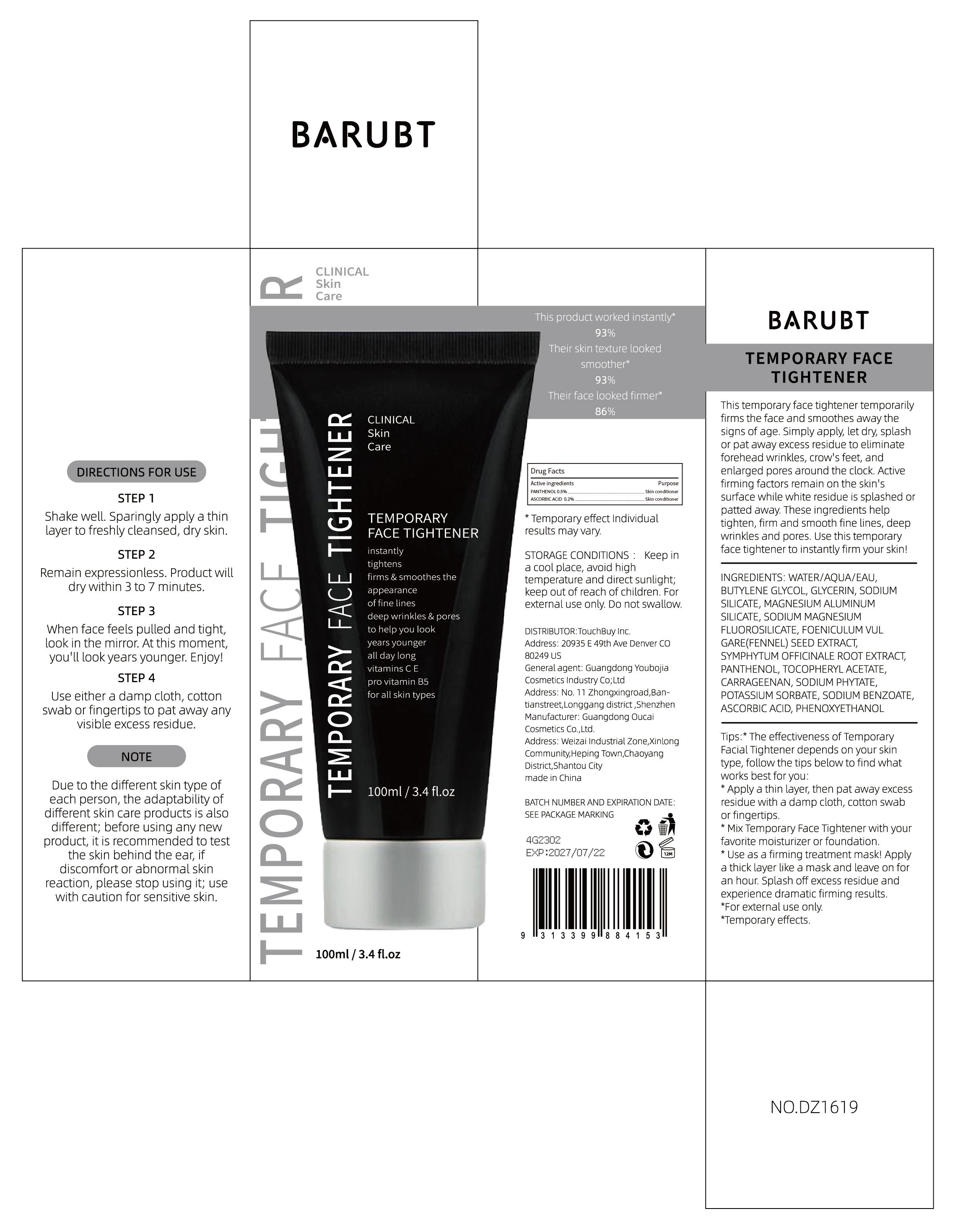 DRUG LABEL: BARUBT TEMPORARY FACE TIGHTENER
NDC: 84712-008 | Form: CREAM
Manufacturer: Guangdong Youbaijia Cosmetic Industry Co., Ltd
Category: otc | Type: HUMAN OTC DRUG LABEL
Date: 20240913

ACTIVE INGREDIENTS: PANTHENOL 0.5 g/100 g; ASCORBIC ACID 0.2 g/100 g
INACTIVE INGREDIENTS: GLYCERIN 2 g/100 g; BUTYLENE GLYCOL 5 g/100 g

ACTIVE INGREDIENT

PANTHENOL 0.5%
ASCORBIC ACID 0.2%

INACTIVE INGREDIENT

WATER/AQUA/EAU
BUTYLENE GLYCOL
GLYCERIN
SODIUMSILICATE
MAGNESIUM ALUMINUMSILICATE
SODIUM MAGNESIUMFLUOROSILCATE
FOENKULUM VULGARE(FENNEL) SEED EXTRACT
SYMPHYTUM OFFICINALE ROOT EXTRACT
TOCOPHERYL ACETATE
CARRAGEENAN
SODIUM PHYTATE
POLASSIUM SORBATE
SODIUM BENZOATE
PHENOXYETHANOL

Do not use on damaged skin.

Keep away from children. Do not swallow.

PURPOSE

Face Tightener

STOP USE

before using any new product, it is recommended to test the skin behind the ear if discomfort or abnormal skin reaction, please stop using it

QUESTIONS

Contact name: Jessie Peng
Company phone number: +1 818 579 7288
Company e-mail: jessie@registeragentllc.com

WHEN USING

keep out of eyes. Rinse with water to remove.

WARNINGS

Due to the different skin type of each person, the adaptability of different skin care products is also different; before using any new product, it is recommended to test the skin behind the ear if discomfort or abnormal skin reaction, please stop using it; use with caution for sensitive skin.

STORAGE AND HANDLING

STORAGE CONDITIONS :Keep in a cool place, avoid high temperature and direct sunlight

INDICATIONS AND USAGE

This temporary face tightener temporarily firms the face and smoothes away the signs of age. Simply apply, let dry, splash or pat away excess residue to eliminate forehead wrinkles, crow's feet, and enlarged pores around the clock. Active firming factors remain on the skin's surface while white residue is splashed or patted away. These ingredients help tighten, firm and smooth fine lines, deep wrinkles and pores. Use this temporary face tightener to instantly firm your skin!

DOSAGE AND ADMINISTRATION

STEP 1

Shake well. Sparingly apply a thin layer to freshly cleansed, dry skin.
STEP 2
Remain expressionless. Product will dry within 3 to 7 minutes.
STEP 3
when face feels pulled and tight,look in the mirror. At this moment you'll look years younger. Enjoy!
STEP 4
Use either a damp cloth, cotton swab or fingertips to pat away any visible excess residue